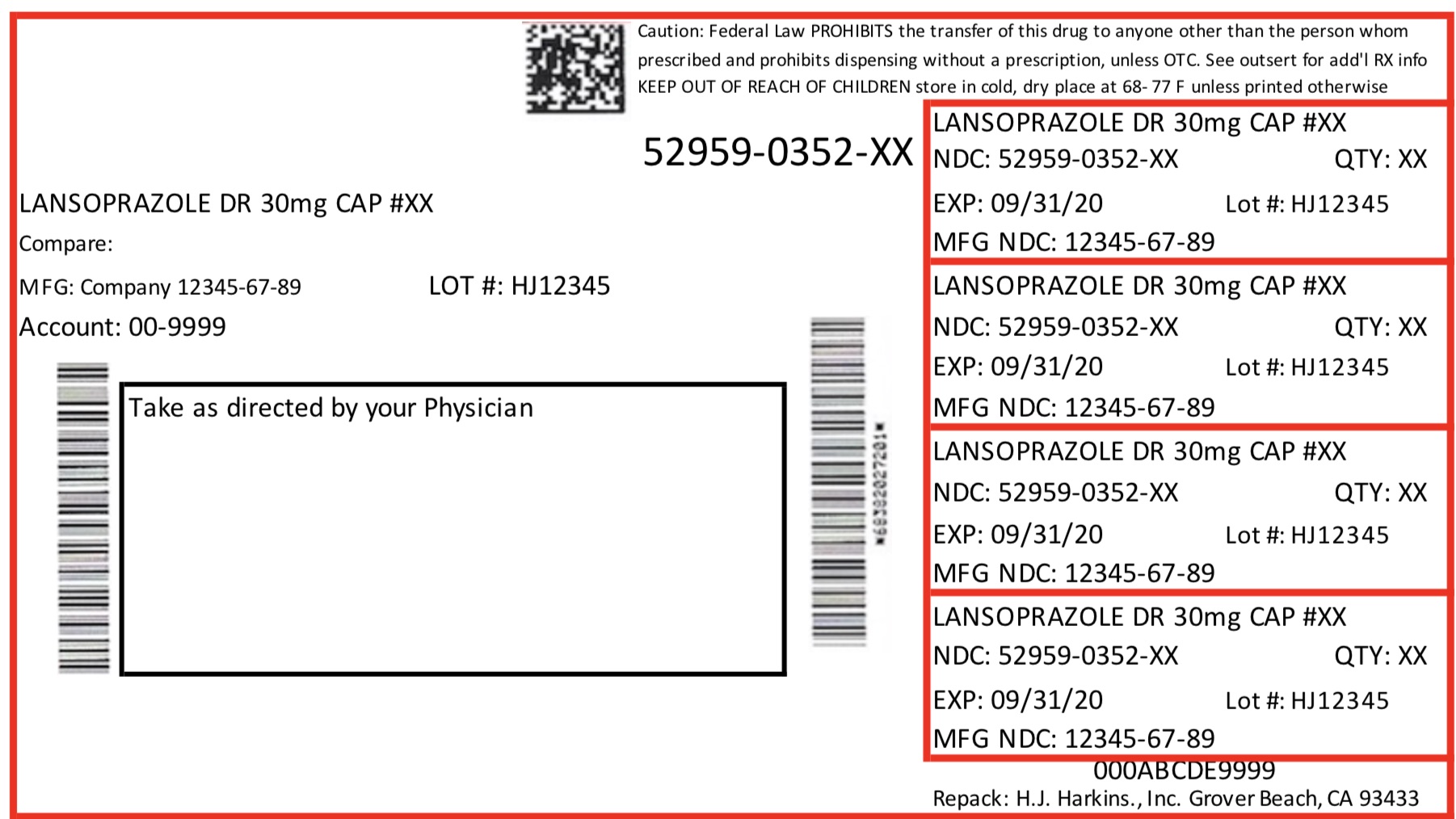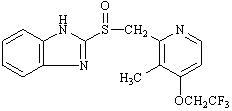 DRUG LABEL: LANSOPRAZOLE
NDC: 52959-352 | Form: CAPSULE, DELAYED RELEASE
Manufacturer: H.J. Harkins Co., Inc
Category: prescription | Type: HUMAN PRESCRIPTION DRUG LABEL
Date: 20180315

ACTIVE INGREDIENTS: LANSOPRAZOLE 30 mg/1 1
INACTIVE INGREDIENTS: POLYSORBATE 80; AMMONIA; HYDROXYPROPYL CELLULOSE (TYPE H); SHELLAC; HYDROXYPROPYL CELLULOSE, LOW SUBSTITUTED; POLYETHYLENE GLYCOLS; PROPYLENE GLYCOL; STARCH, CORN; FD&C BLUE NO. 2; SUCROSE; RAW SUGAR; TITANIUM DIOXIDE; TALC; FERRIC OXIDE RED; SODIUM LAURYL SULFATE; MAGNESIUM CARBONATE; METHACRYLIC ACID - ETHYL ACRYLATE COPOLYMER (1:1) TYPE A; GELATIN; FERRIC OXIDE YELLOW

Indictaions & Usage

1.1 Short-Term Treatment of Active Duodenal Ulcer

Lansoprazole delayed-release capsules are indicated for short-term treatment (for 4 weeks) for healing and symptom relief of active duodenal ulcer. [See CLINICAL STUDIES (14)]

1.2 H. pylori Eradication to Reduce the Risk of Duodenal Ulcer Recurrence

Triple Therapy: Lansoprazole delayed-release capsules /amoxicillin /clarithromycin

Lansoprazole delayed-release capsules in combination with amoxicillin plus clarithromycin as triple therapy is indicated for the treatment of patients with H. pylori infection and duodenal ulcer disease (active or one-year history of a duodenal ulcer) to eradicate H. pylori. Eradication of H. pylori has been shown to reduce the risk of duodenal ulcer recurrence. [See CLINICAL STUDIES (14)]

Please refer to the full prescribing information for amoxicillin and clarithromycin.

Dual Therapy: Lansoprazole delayed-release capsules /amoxicillin

Dual Therapy: Lansoprazole delayed-release capsules /amoxicillinLansoprazole delayed-release capsules in combination with amoxicillin as dual therapy is indicated for the treatment of patients with H. pylori infection and duodenal ulcer disease (active or one-year history of a duodenal ulcer) who are either allergic or intolerant to clarithromycin or in whom resistance to clarithromycin is known or suspected (see the clarithromycin package insert, MICROBIOLOGY section). Eradication of H. pylori has been shown to reduce the risk of duodenal ulcer recurrence. [See CLINICAL STUDIES (14)]

Please refer to the full prescribing information for amoxicillin.

1.3 Maintenance of Healed Duodenal Ulcers

Lansoprazole delayed-release capsules are indicated to maintain healing of duodenal ulcers. Controlled studies do not extend beyond 12 months. [See CLINICAL STUDIES (14)]

1.4 Short-Term Treatment of Active Benign Gastric Ulcer

Lansoprazole delayed-release capsules are indicated for short-term treatment (up to 8 weeks) for healing and symptom relief of active benign gastric ulcer. [See CLINICAL STUDIES (14)]

1.5 Healing of NSAID-Associated Gastric Ulcer

Lansoprazole delayed-release capsules are indicated for the treatment of NSAID-associated gastric ulcer in patients who continue NSAID use. Controlled studies did not extend beyond 8 weeks. [See CLINICAL STUDIES (14)]

1.6 Risk Reduction of NSAID-Associated Gastric Ulcer

Lansoprazole delayed-release capsules are indicated for reducing the risk of NSAID-associated gastric ulcers in patients with a history of a documented gastric ulcer who require the use of an NSAID. Controlled studies did not extend beyond 12 weeks. [See CLINICAL STUDIES (14)]

1.7 Gastroesophageal Reflux Disease (GERD)

Short-Term Treatment of Symptomatic GERD

Lansoprazole delayed-release capsules is indicated for the treatment of heartburn and other symptoms associated with GERD for upto 8 weeks. [See CLINICAL STUDIES (14)]

Short-Term Treatment of Erosive Esophagitis

Lansoprazole delayed-release capsules is indicated for short-term treatment (up to 8 weeks) for healing and symptom relief of all grades of erosive esophagitis.

For patients who do not heal with lansoprazole delayed-release capsules for 8 weeks (5 to10%), it may be helpful to give an additional 8 weeks of treatment. If there is a recurrence of erosive esophagitis an additional 8-week course of lansoprazole delayed-release capsules may be considered. [See CLINICAL STUDIES (14)]

1.8 Maintenance of Healing of Erosive Esophagitis (EE)

Lansoprazole delayed-release capsules are indicated to maintain healing of erosive esophagitis. Controlled studies did not extend beyond 12 months. [See CLINICAL STUDIES (14)]

1.9 Pathological Hypersecretory Conditions Including Zollinger-Ellison Syndrome (ZES)

Lansoprazole delayed-release capsules are indicated for the long-term treatment of pathological hypersecretory conditions, including Zollinger-Ellison syndrome. [See CLINICAL STUDIES (14)]

Dosage Forms & Strengths

Lansoprazole delayed release capsules USP, 15 mg are white to pale yellow colored enteric coated pellets filled in size ‘3’ hard gelatin capsules with opaque pink colored cap and opaque green colored body, imprinted ‘RDY’ on cap and ‘LAN’ on body with white ink.
Lansoprazole delayed release capsules USP, 30 mg are white to pale yellow colored enteric coated pellets filled in size ‘1’ hard gelatin capsules with opaque pink colored cap and opaque black colored body, imprinted ‘RDY’ on cap and ‘399’ on body with white ink.

Contraindications

Lansoprazole delayed-release capsules are contraindicated in patients with known severe hypersensitivity to any component of the formulation of lansoprazole delayed-release capsules. Hypersensitivity reactions may include anaphylaxis, anaphylactic shock, angioedema, bronchospasm, acute interstitial nephritis, and urticaria [see Adverse Reactions (6)].

Warnings & Precautions

5.1 Gastric Malignancy

Symptomatic response to therapy with lansoprazole does not preclude the presence of gastric malignancy.

5.2 Acute Interstitial Nephritis

Acute interstitial nephritis has been observed in patients taking PPIs including lansoprazole. Acute interstitial nephritis may occur at any point during PPI therapy and is generally attributed to an idiopathic hypersensitivity reaction. Discontinue lansoprazole delayed-release capsules if acute interstitial nephritis develops [see Contraindications (4)].

5.3 Cyanocobalamin (vitamin B12) Deficiency

Daily treatment with any acid-suppressing medications over a long period of time (e.g., longer than 3 years) may lead to malabsorption of cyanocobalamin (vitamin B12) caused by hypo- or achlorhydria. Rare reports of cyanocobalamin deficiency occurring with acid-suppressing therapy have been reported in the literature. This diagnosis should be considered if clinical symptoms consistent with cyanocobalamin deficiency are observed.

5.4 Clostridium difficile Associated Diarrhea

Published observational studies suggest that proton pump inhibitor (PPI) therapy like lansoprazole delayed-release capsules may be associated with an increased risk of Clostridium difficile associated diarrhea (CDAD), especially in hospitalized patients. This diagnosis should be considered for diarrhea that does not improve [see Adverse Reactions (6.2)].

Patients should use the lowest dose and shortest duration of PPI therapy appropriate to the condition being treated.

CDAD has been reported with use of nearly all antibacterial agents. For more information specific to antibacterial agents (clarithromycin and amoxicillin) indicated for use in combination with lansoprazole delayed release capsules, refer to WARNINGS and PRECAUTIONS sections of those package inserts.

5.5 Bone Fracture

Several published observational studies suggest that PPI therapy may be associated with an increased risk for osteoporosis-related fractures of the hip, wrist or spine. The risk of fracture was increased in patients who received high-dose, defined as multiple daily doses, and long-term PPI therapy (a year or longer). Patients should use the lowest dose and shortest duration of PPI therapy appropriate to the condition being treated. Patients at risk for osteoporosis-related fractures should be managed according to established treatment guidelines [see DOSAGE AND ADMINISTRATION (2) and ADVERSE REACTIONS (6.2)].

5.6 Hypomagnesemia

Hypomagnesemia, symptomatic and asymptomatic, has been reported rarely in patients treated with PPIs for at least three months, in most cases after a year of therapy. Serious adverse events include tetany, arrhythmias, and seizures. In most patients, treatment of hypomagnesemia required magnesium replacement and discontinuation of the PPI.

For patients expected to be on prolonged treatment or who take PPIs with medications such as digoxin or drugs that may cause hypomagnesemia (e.g., diuretics), health care professionals may consider monitoring magnesium levels prior to initiation of PPI treatment and periodically [see Adverse Reactions (6.2)].

5.7 Concomitant use of lansoprazole delayed-release capsules with Methotrexate

Literature suggests that concomitant use of PPIs with methotrexate (primarily at high dose; see methotrexate prescribing information) may elevate and prolong serum levels of methotrexate and/or its metabolite, possibly leading to methotrexate toxicities. In high-dose methotrexate administration, a temporary withdrawal of the PPI may be considered in some patients [see Drug Interactions (7.6)and Clinical Pharmacology (12.3)].

Adverse Reactions

6.1 Clinical

Worldwide, over 10,000 patients have been treated with lansoprazole delayed-release capsules in Phase 2 or Phase 3 clinical trials involving various dosages and durations of treatment. In general, lansoprazole delayed-release capsules treatment has been well-tolerated in both short-term and long-term trials.

Because clinical trials are conducted under widely varying conditions, adverse reaction rates observed in the clinical trials of a drug cannot be directly compared to rates in the clinical trials of another drug and may not reflect the rates observed in clinical practice.

The following adverse reactions were reported by the treating physician to have a possible or probable relationship to drug in 1% or more of lansoprazole delayed-release capsules-treated patients and occurred at a greater rate in lansoprazole delayed-release capsules-treated patients than placebo-treated patients in Table 1.

Table 1: Incidence of Possibly or Probably Treatment-Related Adverse Reactions in Short-Term, Placebo-Controlled lansoprazole delayed-release capsules Studies
Body System/Adverse Event. lansoprazole delayed-release capsules Placebo (N= 2768) (n=2768) % (n=1023) %
Body as a Whole
Abdominal Pain 2.1 1.2
Digestive System
Constipation 1 0 .4
Diarrhea 3.8 2.3
Nausea 1.3 1.2

Headache was also seen at greater than 1% incidence but was more common on placebo. The incidence of diarrhea was similar between patients who received placebo and patients who received 15 mg and 30 mg of lansoprazole delayed-release capsules, but higher in the patients who received 60 mg of lansoprazole delayed-release capsules (2.9%, 1.4%, 4.2%, and 7.4%, respectively).

The most commonly reported possibly or probably treatment-related adverse event during maintenance therapy was diarrhea.

In the risk reduction study of lansoprazole delayed-release capsules for NSAID-associated gastric ulcers, the incidence of diarrhea for patients treated with lansoprazole delayed-release capsules, misoprostol, and placebo was 5%, 22%, and 3%, respectively.

Another study for the same indication, where patients took either a COX-2 inhibitor or lansoprazole and naproxen, demonstrated that the safety profile was similar to the prior study. Additional reactions from this study not previously observed in other clinical trials with lansoprazole delayed-release capsules included contusion, duodenitis, epigastric discomfort, esophageal disorder, fatigue, hunger, hiatal hernia, hoarseness, impaired gastric emptying, metaplasia, and renal impairment.

Additional adverse experiences occurring in less than 1% of patients or subjects who received lansoprazole delayed-release capsules in domestic trials are shown below:

Body as a Whole – abdomen enlarged, allergic reaction, asthenia, back pain, candidiasis, carcinoma, chest pain (not otherwise specified), chills, edema, fever, flu syndrome, halitosis, infection (not otherwise specified), malaise, neck pain, neck rigidity, pain, pelvic pain

Cardiovascular System - angina, arrhythmia, bradycardia, cerebrovascular accident/cerebral infarction, hypertension/hypotension, migraine, myocardial infarction, palpitations, shock (circulatory failure), syncope, tachycardia, vasodilation

Digestive System – abnormal stools, anorexia, bezoar, cardiospasm, cholelithiasis, colitis, dry mouth, dyspepsia, dysphagia, enteritis, eructation, esophageal stenosis, esophageal ulcer, esophagitis, fecal discoloration, flatulence, gastric nodules/fundic gland polyps, gastritis, gastroenteritis, gastrointestinal anomaly, gastrointestinal disorder, gastrointestinal hemorrhage, glossitis, gum hemorrhage, hematemesis, increased appetite, increased salivation, melena, mouth ulceration, nausea and vomiting, nausea and vomiting and diarrhea, gastrointestinal moniliasis, rectal disorder, rectal hemorrhage, stomatitis, tenesmus, thirst, tongue disorder, ulcerative colitis, ulcerative stomatitis

Endocrine System - diabetes mellitus, goiter, hypothyroidism

Hemic and Lymphatic System - anemia, hemolysis, lymphadenopathy

Metabolism and Nutritional Disorders - avitaminosis, gout, dehydration, hyperglycemia/hypoglycemia, peripheral edema, weight gain/loss

Musculoskeletal System - arthralgia, arthritis, bone disorder, joint disorder, leg cramps, musculoskeletal pain, myalgia, myasthenia, ptosis, synovitis

Nervous System – abnormal dreams, agitation, amnesia, anxiety, apathy, confusion, convulsion, dementia, depersonalization, depression, diplopia, dizziness, emotional lability, hallucinations, hemiplegia, hostility aggravated, hyperkinesia, hypertonia, hypesthesia, insomnia, libido decreased/increased, nervousness, neurosis, paresthesia, sleep disorder, somnolence, thinking abnormality, tremor, vertigo

Respiratory System - asthma, bronchitis, cough increased, dyspnea, epistaxis, hemoptysis, hiccup, laryngeal neoplasia, lung fibrosis, pharyngitis, pleural disorder, pneumonia, respiratory disorder, upper respiratory inflammation/infection, rhinitis, sinusitis, stridor

Skin and Appendages - acne, alopecia, contact dermatitis, dry skin, fixed eruption, hair disorder, maculopapular rash, nail disorder, pruritus, rash, skin carcinoma, skin disorder, sweating, urticaria

Special Senses – abnormal vision, amblyopia, blepharitis, blurred vision, cataract, conjunctivitis, deafness, dry eyes, ear/eye disorder, eye pain, glaucoma, otitis media, parosmia, photophobia, retinal degeneration/disorder, taste loss, taste perversion, tinnitus, visual field defect

Urogenital System - abnormal menses, breast enlargement, breast pain, breast tenderness, dysmenorrhea, dysuria, gynecomastia, impotence, kidney calculus, kidney pain, leukorrhea, menorrhagia, menstrual disorder, penis disorder, polyuria, testis disorder, urethral pain, urinary frequency, urinary retention, urinary tract infection, urinary urgency, urination impaired, vaginitis.

6.2 Postmarketing Experience

Additional adverse experiences have been reported since lansoprazole delayed-release capsules has been marketed. The majority of these cases are foreign-sourced and a relationship to lansoprazole delayed-release capsules has not been established. Because these reactions were reported voluntarily from a population of unknown size, estimates of frequency cannot be made. These events are listed below by COSTART body system.

Body as a Whole – anaphylactic/anaphylactoid reactions; Digestive System - hepatotoxicity, pancreatitis, vomiting; Hemic and Lymphatic System - agranulocytosis, aplastic anemia, hemolytic anemia, leukopenia, neutropenia, pancytopenia, thrombocytopenia, and thrombotic thrombocytopenic purpura; Infections and Infestations – Clostridium difficile associated diarrhea; Metabolism and Nutritional Disorders – hypomagnesemia; Musculoskeletal System - bone fracture,myositis; Skin and Appendages – severe dermatologic reactions including erythema multiforme, Stevens-Johnson syndrome, toxic epidermal necrolysis (some fatal); Special Senses - speech disorder; Urogenital System – interstitial nephritis, urinary retention.

6.3 Combination Therapy with Amoxicillin and Clarithromycin

In clinical trials using combination therapy with lansoprazole delayed-release capsules plus amoxicillin and clarithromycin, and lansoprazole delayed-release capsules plus amoxicillin, no adverse reactions peculiar to these drug combinations were observed. Adverse reactions that have occurred have been limited to those that had been previously reported with lansoprazole delayed-release capsules, amoxicillin, or clarithromycin.

Triple Therapy: Lansoprazole delayed-release capsules /amoxicillin/clarithromycin

The most frequently reported adverse reactions for patients who received triple therapy for 14 days were diarrhea (7%), headache (6%), and taste perversion (5%). There were no statistically significant differences in the frequency of reported adverse reactions between the 10 and 14 day triple therapy regimens. No treatment-emergent adverse reactions were observed at significantly higher rates with triple therapy than with any dual therapy regimen.

Dual Therapy: Lansoprazole delayed-release capsules /amoxicillin

The most frequently reported adverse reactions for patients who received lansoprazole delayed-release capsules three times daily plus amoxicillin three times daily dual therapy were diarrhea (8%) and headache (7%). No treatment-emergent adverse reactions were observed at significantly higher rates with lansoprazole delayed-release capsules three times daily plus amoxicillin three times daily dual therapy than with lansoprazole delayed-release capsules alone.

For information about adverse reactions with antibacterial agents (amoxicillin and clarithromycin) indicated in combination with lansoprazole delayed-release capsules, refer to the ADVERSE REACTIONS section of their package inserts.

6.4 Laboratory Values

The following changes in laboratory parameters in patients who received lansoprazole delayed-release capsules were reported as adverse reactions:

Abnormal liver function tests, increased SGOT (AST), increased SGPT (ALT), increased creatinine, increased alkaline phosphatase, increased globulins, increased GGTP, increased/decreased/abnormal WBC, abnormal AG ratio, abnormal RBC, bilirubinemia, blood potassium increased, blood urea increased, crystal urine present, eosinophilia, hemoglobin decreased, hyperlipemia, increased/decreased electrolytes, increased/decreased cholesterol, increased glucocorticoids, increased LDH, increased/decreased/abnormal platelets, increased gastrin levels and positive fecal occult blood. Urine abnormalities such as albuminuria, glycosuria, and hematuria were also reported. Additional isolated laboratory abnormalities were reported.

In the placebo controlled studies, when SGOT (AST) and SGPT (ALT) were evaluated, 0.4% (4/978) and 0.4% (11/2677) patients, who received placebo and lansoprazole delayed-release capsules, respectively, had enzyme elevations greater than three times the upper limit of normal range at the final treatment visit. None of these patients who received lansoprazole delayed-release capsules reported jaundice at any time during the study.

In clinical trials using combination therapy with lansoprazole delayed-release capsules plus amoxicillin and clarithromycin, and lansoprazole delayed-release capsules plus amoxicillin, no increased laboratory abnormalities particular to these drug combinations were observed.

For information about laboratory value changes with antibacterial agents (amoxicillin and clarithromycin) indicated in combination with lansoprazole delayed-release capsules, refer to the ADVERSE REACTIONS section of their package inserts.

Drug Interactions

7.1 Drugs with pH-Dependent Absorption Kinetics

Due to its effects on gastric acid secretion, lansoprazole can reduce the absorption of drugs where gastric pH is an important determinant of their bioavailability. Like with other drugs that decrease the intragastric acidity, the absorption of drugs such as ampicillin esters, ketoconazole, atazanavir, iron salts, erlotinib, and mycophenolate mofetil (MMF) can decrease, while the absorption of drugs such as digoxin can increase during treatment with lansoprazole delayed-release capsules [see Clinical Pharmacology (12.3)].

Lansoprazole delayed-release capsules are likely to substantially decrease the systemic concentrations of the HIV protease inhibitor atazanavir, which is dependent upon the presence of gastric acid for absorption, and may result in a loss of therapeutic effect of atazanavir and the development of HIV resistance. Therefore, lansoprazole delayed-release capsules should not be co-administered with atazanavir [see Clinical Pharmacology (12.3)].

Co-administration of PPIs in healthy subjects and in transplant patients receiving MMF has been reported to reduce the exposure to the active metabolite, mycophenolic acid (MPA), possibly due to a decrease in MMF solubility at an increased gastric pH. The clinical relevance of reduced MPA exposure on organ rejection has not been established in transplant patients receiving PPIs and MMF. Use lansoprazole delayed-release capsules with caution in transplant patients receiving MMF.

7.2 Warfarin

In a study of healthy subjects, co-administration of single or multiple 60 mg doses of lansoprazole delayed-release capsules and warfarin did not affect the pharmacokinetics of warfarin nor prothrombin time (see CLINICAL PHARMACOLOGY (12.3). However, there have been reports of increased INR and prothrombin time in patients receiving PPIs and warfarin concomitantly. Increases in INR and prothrombin time may lead to abnormal bleeding and even death. Patients treated with PPIs and warfarin concomitantly may need to be monitored for increases in INR and prothrombin time. [See CLINICAL PHARMACOLOGY (12.3)]

7.3 Tacrolimus

Concomitant administration of lansoprazole and tacrolimus may increase whole blood levels of tacrolimus, especially in transplant patients who are intermediate or poor metabolizers of CYP2C19.

7.4 Theophylline

A minor increase (10%) in the clearance of theophylline was observed following the administration of lansoprazole delayed-release capsules concomitantly with theophylline. Although the magnitude of the effect on theophylline clearance is small, individual patients may require additional titration of their theophylline dosage when lansoprazole delayed-release capsules is started or stopped to ensure clinically effective blood levels. [See CLINICAL PHARMACOLOGY (12.3)]

7.5 Clopidogrel

Concomitant administration of lansoprazole and clopidogrel in healthy subjects had no clinically important effect on exposure to the active metabolite of clopidogrel or clopidogrel-induced platelet inhibition [see CLINICAL PHARMACOLOGY (12.3)]. No dose adjustment of clopidogrel is necessary when administered with an approved dose of lansoprazole delayed-release capsules.

7.6 Methotrexate

Case reports, published population pharmacokinetic studies, and retrospective analyses suggest that concomitant administration of PPIs and methotrexate (primarily at high dose; see methotrexate prescribing information) may elevate and prolong serum levels of methotrexate and/or its metabolite hydroxymethotrexate. However, no formal drug interaction studies of high dose methotrexate with PPIs have been conducted [see Warnings and Precautions (5.7)].

In a study of rheumatoid arthritis patients receiving low-dose methotrexate, lansoprazole delayed-release capsules and naproxen, no effect on pharmacokinetics of methotrexate was observed [see Clinical Pharmacology (12.3)].

7.7 Combination Therapy with Clarithromycin

Concomitant administration of clarithromycin with other drugs can lead to serious adverse reactions due to drug interactions [see Warnings and Precautions in prescribing information for clarithromycin]. Because of these drug interactions, clarithromycin is contraindicated for co-administration with certain drugs [see Contraindications in prescribing information for clarithromycin].

For information on drug interactions for amoxicillin or clarithromycin, refer to their full prescribing information, DRUG INTERACTIONS sections.

Overdosage

Lansoprazole delayed-release capsules are not removed from the circulation by hemodialysis. In one reported overdose, a patient consumed 600 mg of lansoprazole delayed-release capsules with no adverse reaction. Oral lansoprazole delayed-release capsules doses up to 5000 mg/kg in rats [approximately 1300 times the 30 mg human dose based on body surface area BSA)] and in mice (about 675.7 times the 30 mg human dose based on (BSA) did not produce deaths or any clinical signs.

Description

The active ingredient in lansoprazole delayed-release capsules USP is lansoprazole USP, a substituted benzimidazole, 2-[[[3-methyl-4-(2,2,2-trifluoroethoxy)-2-pyridyl] methyl] sulfinyl] benzimidazole, a compound that inhibits gastric acid secretion. Its empirical formula is C16H14F3N3O2S with a molecular weight of 369.37. Lansoprazole USP has the following structure:

Lansoprazole USP is a white to brownish-white powder which melts with decomposition at approximately 166°C. Lansoprazole USP is freely soluble in dimethylformamideand practically insoluble in water.

Lansoprazole USP is stable when exposed to light for up to two months. The rate of degradation of the compound in aqueous solution increases with decreasing pH. The degradation half-life of the drug substance in aqueous solution at 25°C is approximately 0.5 hour at pH 5.0 and approximately 18 hours at pH 7.0.

Lansoprazole USP is supplied as delayed-release capsules.

The delayed-release capsules are available in two dosage strengths: 15 mg and 30 mg of lansoprazole USP per capsule. Each delayed-release capsule contains enteric-coated granules consisting of 15 mg or 30 mg of lansoprazole USP (active ingredient) and the following inactive ingredients: ammonium hydroxide, hydroxypropyl cellulose, low substituted hydroxypropyl cellulose, magnesium carbonate, methacrylic acid copolymer, polyethylene glycol, polysorbate 80, propylene glycol, shellac, simethicone, starch, sucrose, sugar spheres, talc, and titanium dioxide.

Components of the gelatin capsule include gelatin, iron oxide red, iron oxide yellow, FD&C Blue 2, sodium lauryl sulphate and titanium dioxide for 15 mg capsules and gelatin, iron oxide black, iron oxide red, iron oxide yellow, sodium lauryl sulphate and titanium dioxide for 30 mg capsules.

Nonclinical Toxicology

13.1 Carcinogenesis, Mutagenesis, Impairment of Fertility

In two 24-month carcinogenicity studies, Sprague-Dawley rats were treated with oral lansoprazole doses of 5 to 150 mg/kg/day –about 1 to 40 times the exposure on a body surface (mg/m2) basis of a 50 kg person of average height [1.46 m2 body surface area (BSA)] given the recommended human dose of 30 mg/day. Lansoprazole produced dose-related gastric enterochromaffin-like (ECL) cell hyperplasia and ECL cell carcinoids in both male and female rats. It also increased the incidence of intestinal metaplasia of the gastric epithelium in both sexes. In male rats, lansoprazole produced a dose-related increase of testicular interstitial cell adenomas. The incidence of these adenomas in rats receiving doses of 15 to 150 mg/kg/day (4 to 40 times the recommended human dose based on BSA) exceeded the low background incidence (range = 1.4 to 10%) for this strain of rat.

In a 24-month carcinogenicity study, CD-1 mice were treated with oral lansoprazole doses of 15 to 600 mg/kg/day, 2 to 80 times the recommended human dose based on BSA. Lansoprazole produced a dose-related increased incidence of gastric ECL cell hyperplasia. It also produced an increased incidence of liver tumors (hepatocellular adenoma plus carcinoma). The tumor incidences in male mice treated with 300 and 600 mg/kg/day (40 to 80 times the recommended human dose based on BSA) and female mice treated with 150 to 600 mg/kg/day (20 to 80 times the recommended human dose based on BSA) exceeded the ranges of background incidences in historical controls for this strain of mice. Lansoprazole treatment produced adenoma of rete testis in male mice receiving 75 to 600 mg/kg/day (10 to 80 times the recommended human dose based on BSA).

A 26-week p53 (+/-) transgenic mouse carcinogenicity study was not positive.

Lansoprazole was positive in the Ames test and the in vitro human lymphocyte chromosomal aberration assay.Lansoprazole was not genotoxic in the ex vivo rat hepatocyte unscheduled DNA synthesis (UDS) test, the in vivo mouse micronucleus test, or the rat bone marrow cell chromosomal aberration test.

Lansoprazole at oral doses up to 150 mg/kg/day (40 times the recommended human dose based on BSA) was found to have no effect on fertility and reproductive performance of male and female rats.

13.2 Animal Toxicology and/or Pharmacology

Reproductive Toxicology Studies

Reproduction studies have been performed in pregnant rats at oral lansoprazole doses up to 150 mg/kg/day [40 times the recommended human dose (30 mg/day) based on body surface area (BSA)] and pregnant rabbits at oral lansoprazole doses up to 30 mg/kg/day (16 times the recommended human dose based on BSA) and have revealed no evidence of impaired fertility or harm to the fetus due to lansoprazole.

How Supplied

Lansoprazole delayed release capsules USP, 30 mg are white to pale yellow colored enteric coated pellets filled in size ‘1’ hard gelatin capsules with opaque pink colored cap and opaque black colored body, imprinted ‘RDY’ on cap and ‘399’ on body with white ink. They are supplied in bottles of 30’s, 60’s, 90's, 100’s, 500’s and unit dose package of 10 (1 x 10).

Store at 20°–25° C (68°–77° F); [See USP Controlled Room Temperature].

Patient Counseling Information

[See FDA-Approved Medication Guide and Patient Instructions for Use]

Patient should be informed of the following:

Advise patients to immediately report and seek care for diarrhea that does not improve. This may be a sign of Clostridium difficile associated diarrhea [see Warnings and Precautions (5.2)].
Advise patients to immediately report and seek care for any cardiovascular or neurological symptoms including palpitations, dizziness, seizures, and tetany as these may be signs of hypomagnesemia [see Warnings and Precautions (5.4)].

Information for Patients

Lansoprazole is available as a capsule and is available in 15 mg and 30 mg strengths. Directions for use specific to the route and available methods of administration is presented below. [See DOSAGE AND ADMINISTRATION (2.3)]

Lansoprazole should be taken before eating.
Lansoprazole products SHOULD NOT BE CRUSHED OR CHEWED.

Administration Options

1 Lansoprazole Delayed-Release Capsules

Lansoprazole delayed-release capsules should be swallowed whole.
Alternatively, for patients who have difficulty swallowing capsules, lansoprazole delayed-release capsules can be opened and administered as follows:

o Open capsule.

o Sprinkle intact granules on one tablespoon of either applesauce, ENSURE pudding, cottage cheese, yogurt or strained pears.

o Swallow immediately.

Lansoprazole

o Open capsule.

o Sprinkle intact granules into a small volume of either apple juice, orange juice or tomato juice (60 mL – approximately 2 ounces).

o Mix briefly.

o Swallow immediately.

o To ensure complete delivery of the dose, the glass should be rinsed with two or more volumes of juice and the contents swallowed immediately.

Lansoprazole delayed-release capsules – Nasogastric Tube (≥16 French) Administration
For patients who have a nasogastric tube in place, lansoprazole delayed-release capsules can be administered as follows:

o Open capsule.

o Mix intact granules into 40 mL of apple juice. DO NOT USE OTHER LIQUIDS.

o Inject through the nasogastric tube into the stomach.

o Flush with additional apple juice to clear the tube.

USE IN OTHER FOODS AND LIQUIDS HAS NOT BEEN STUDIED CLINICALLY AND IS THEREFORE NOT RECOMMENDED.

Medication Guide

Lansoprazole Delayed-Release Capsules, USP

Read this Medication Guide before you start taking lansoprazole delayed-release capsules and each time you get a refill. There may be new information. This information does not take the place of talking to your doctor about your medical condition or your treatment.

What is the most important information that I should know about lansoprazole delayed-release capsules?

Lansoprazole delayed-release capsules may help your acid-related symptoms, but you could still have serious stomach problems. Talk with your doctor.

Lansoprazole delayed-release capsules can cause serious side effects, including:

Diarrhea. Lansoprazole delayed-release capsules may increase your risk of getting severe diarrhea. This diarrhea may be caused by an infection (Clostridium difficile) in your intestines. Call your doctor right away if you have watery stool, stomach pain, and fever that does not go away.
Bone fractures. People who take multiple daily doses of proton pump inhibitor medicines for a long period of time (a year or longer) may have an increased risk of fractures of the hip, wrist or spine. You should take lansoprazole delayed-release capsules exactly as prescribed, at the lowest dose possible for your treatment and for the shortest time needed. Talk to your doctor about your risk of bone fracture if you take lansoprazole delayed-release capsules.

Lansoprazole delayed-release capsules can have other serious side effects. See “What are the possible side effects of lansoprazole delayed-release capsules?”

What are lansoprazole delayed-release capsules?

Lansoprazole delayed-release capsules are prescription medicine called a proton pump inhibitor (PPI). Lansoprazole delayed-release capsules reduces the amount of acid in your stomach.

Lansoprazole delayed-release capsules are used in adults:

for 4 weeks for the healing and symptom relief of duodenal ulcers. The duodenal area is the area where food passes when it leaves the stomach.
with certain antibiotics to treat an infection called H. pylori. Sometimes H. pylori bacteria can cause duodenal ulcers. The infection needs to be treated to prevent ulcers from coming back.
for continued healing of duodenal ulcers. for up to 8 weeks to heal stomach ulcers.
for up to 8 weeks to heal stomach ulcers in some people taking pain medicines called non-steroidal anti-inflammatory drugs (NSAIDs).
for reducing the risk of stomach ulcers in some people taking NSAIDs.
for up to 8 weeks for the relief of heartburn and other symptoms of gastroesophageal reflux disease (GERD).
GERD happens when acid in your stomach backs up into the tube (esophagus) that connects your mouth to your stomach. This may cause a burning feeling in your chest or throat, sour taste or burping.
for 8 weeks to heal the acid-related damage to the lining of the esophagus (called erosive esophagitis) and to relieve symptoms. If needed, your doctor may prescribe another 8 weeks of lansoprazole delayed-release capsules.
for continued healing of erosive esophagitis.
for the long-term treatment of conditions where your stomach makes too much acid. This includes a condition called Zollinger-Ellison syndrome.

Lansoprazole delayed-release capsules are used in children and adolescents (ages 1 to 17):

for up to 12 weeks to treat GERD and erosive esophagitis in children 1 to 11 years old.
for up to 8 weeks to treat GERD and erosive esophagitis in adolescents 12 to 17 years old.

Lansoprazole delayed-release capsules are not effective for symptoms of GERD in children under the age of 1 year.

Who should not take lansoprazole delayed-release capsules?

Do not take lansoprazole delayed-release capsules if you are allergic to lansoprazole or any of the other ingredients in lansoprazole delayed-release capsules. See the end of this Medication Guide for a complete list of ingredients in lansoprazole delayed-release capsules.

What should I tell my doctor before taking lansoprazole delayed-release capsules?

Before you take lansoprazole delayed-release capsules, tell your doctor if you:

have been told that you have low magnesium levels in your blood.
have liver problems
have any other medical conditions
are pregnant or plan to become pregnant. It is not known if lansoprazole delayed-release capsules will harm your unborn baby.
are breastfeeding or plan to breastfeed. It is not known if lansoprazole delayed-release capsules passes into your breast milk. You and your doctor should decide if you will take lansoprazole delayed-release capsules or breastfeed. You should not do both. Talk to your doctor about the best way to feed your baby if you take lansoprazole delayed-release capsules.

Tell your doctor about all the medicines you take, including prescription and non-prescription drugs, vitamins, and herbal supplements. Lansoprazole delayed-release capsules may affect how other medicines work, and other medicines may affect how lansoprazole delayed-release capsules works.

Especially tell your doctor if you take:

atazanavir (Reyataz)
erlotinib (Tarceva)
digoxin (Lanoxin)
a product that contains iron
ketoconazole (Nizoral)
warfarin (Coumadin, Jantoven)
tacrolimus (Prograf)
theophylline (Theo-24, Elixophyllin, Theochron, Theolair)
an antibiotic that contains ampicillin or clarithromycin
methotrexate
mycophenolate mofetil (Cellcept)

Ask your doctor or pharmacist for a list of these medicines if you are not sure.

Know the medicines that you take. Keep a list of them to show your doctor and pharmacist when you get a new medicine.

How should I take lansoprazole delayed-release capsules?

Take lansoprazole delayed-release capsules exactly as prescribed by your doctor.
Do not change your dose or stop taking lansoprazole delayed-release capsules without talking to your doctor.
You should take lansoprazole delayed-release capsules before eating.
Lansoprazole Delayed-Release Capsules:

You should swallow lansoprazole delayed-release capsules whole.
Do not crush or chew lansoprazole delayed-release capsules.
If you have trouble swallowing a whole capsule, you can open the capsule and take the contents with certain foods or juices. See the “Instructions for Use” at the end of this Medication Guide for instructions on how to take lansoprazole delayed-release capsules with certain foods and juices.
See the “Instructions for Use” at the end of this Medication Guide for instructions on how to mix and give lansoprazole delayed-release capsules through a nasogastric tube.

If you miss a dose, take it as soon as you remember. If it is almost time for your next dose, skip the missed dose. Just take the next dose at your regular time. Do not take 2 doses at the same time.
If you take too much lansoprazole delayed-release capsules, call your doctor right away.

What are the possible side effects of lansoprazole delayed-release capsules?

Lansoprazole delayed-release capsules can cause serious side effects, including:

See “What is the most important information that I should know about lansoprazole delayed-release capsules?”

Vitamin B12 deficiency. Lansoprazole delayed-release capsules reduces the amount of acid in your stomach. Stomach acid is needed to absorb vitamin B12 properly. Talk with your doctor about the possibility of vitamin B12 deficiency if you have been on lansoprazole delayed-release capsules for a long time (more than 3 years).
Low magnesium levels in your body. This problem can be serious. Low magnesium can happen in some people who take a proton pump inhibitor medicine for at least 3 months. If low magnesium levels happen, it is usually after a year of treatment. You may or may not have symptoms of low magnesium.

Tell your doctor right away if you develop any of these symptoms:

seizures
dizziness
abnormal or fast heartbeat
jitteriness
jerking movements or shaking (tremors)
muscle weakness
spasms of the hands and feet
cramps or muscle aches
spasm of the voice box

Your doctor may check the level of magnesium in your body before you start taking lansoprazole delayed-release capsules, or during treatment; if you will be taking lansoprazole delayed-release capsules for a long period of time.

The most common side effects of lansoprazole delayed-release capsules in adults and children include:

diarrhea
stomach pain
nausea
constipation
headache

Other side effects:

Serious allergic reactions. Tell your doctor if you get any of the following symptoms with lansoprazole delayed-release capsules.

rash face swelling throat tightness difficulty breathing

Your doctor may stop lansoprazole delayed-release capsules if these symptoms happen.

Tell your doctor if you have any side effect that bothers you or that does not go away.

These are not all the possible side effects of lansoprazole delayed-release capsules. For more information, ask your doctor or pharmacist. Call your doctor for medical advice about side effects. You may report side effects to FDA at 1-800-FDA-1088.

How should I store lansoprazole delayed-release capsules?

Store lansoprazole delayed-release capsules at room temperature between 20° to 25° C (68° to 77° F)

Keep lansoprazole delayed-release capsules and all medicines out of the reach of children.

General information about lansoprazole delayed-release capsules

Medicines are sometimes prescribed for conditions other than those listed in a Medication Guide. Do not use lansoprazole delayed-release capsules for conditions for which it was not prescribed. Do not give lansoprazole delayed-release capsules to other people, even if they have the same symptoms you have. It may harm them.

This Medication Guide summarizes the most important information about lansoprazole delayed-release capsules. If you would like more information, talk with your doctor. You can ask your doctor or pharmacist for information about lansoprazole delayed-release capsules that is written for healthcare professionals.

For more information, call 1-888-375-3784.

What are the ingredients in lansoprazole delayed-release capsules?

Active ingredient: lansoprazole.

Inactive ingredients in lansoprazole delayed-release capsules:

Ammonium hydroxide, hydroxypropyl cellulose, low substituted hydroxypropyl cellulose, magnesium carbonate, methacrylic acid copolymer, polyethylene glycol, polysorbate 80, propylene glycol, shellac, simethicone, starch, sucrose, sugar spheres, talc, and titanium dioxide.

Components of the gelatin capsule include gelatin, iron oxide red, iron oxide yellow, FD&C Blue 2, sodium lauryl sulphate and titanium dioxide for 15 mg capsules and gelatin, iron oxide black, iron oxide red, iron oxide yellow, sodium lauryl sulphate and titanium dioxide for 30 mg capsules.

This Medication Guide has been approved by the U.S. Food and Drug Administration.

Patient Instructions for Use

Lansoprazole Delayed-Release Capsules USP

Lansoprazole Delayed-Release Capsules

Swallow lansoprazole delayed-release capsules whole. Do not crush or chew them.
You should take lansoprazole delayed-release capsules before eating.

Lansoprazole Delayed-Release Capsule with certain food:

You can only use applesauce, ENSURE pudding, cottage cheese, yogurt or strained pears.

1. Open the capsule.

2. Sprinkle the granules on 1 tablespoon of either applesauce, ENSURE pudding, cottage cheese, yogurt or strained pears.

3. Swallow right away.

Lansoprazole Delayed-Release Capsule with certain juices:

You can only use apple juice, orange juice or tomato juice.

1 Open the capsule.

2 Sprinkle the granules into 60 mL (about ¼ cup) of either apple juice, orange juice or tomato juice.

3 Stir.

4 Swallow right away.

5 To make sure that the entire dose is taken, rinse the glass with 1/2 cup or more of juice to get out any leftover granules. Swallow the juice right away.

Lansoprazole Delayed-Release Capsules through a nasogastric tube (NG tube) 16 French or larger, as prescribed by your doctor:

You can only use apple juice.

1 Open the capsule and empty the granules into a syringe.

2 Do not break or crush the granules.

3 Mix with 40 mL of apple juice. Do not use other liquids.

4 Attach the syringe to the NG tube and give the medicine in the syringe through the NG tube into the stomach.

5 After giving the granules, flush the NG tube with more apple juice to clear the tube.

Lansoprazole delayed-release capsules should not be used in foods or liquids not listed above.

How should I store lansoprazole delayed-release capsules?

Store lansoprazole delayed-release capsules at room temperature between 20° to 25° C (68° to 77° F)

Keep lansoprazole delayed-release capsules and all medicines out of the reach of children.

This instruction for Use has been approved by the U.S. Food and Drug Administration.

To reorder additional Medication Guides, please contact Dr. Reddy's Customer Service at 1-866-733-3952.

All trademark names are the property of their respective owners.

Rx Only

Manufactured by:

Dr. Reddy’s Laboratories Limited

Bachupally – 500 090 INDIA

Revised: 0115

Dosage & Administration

Lansoprazole is available as a capsule, and is available in 15 mg and 30 mg strengths. Directions for use specific to the route and available methods of administration is presented below. Lansoprazole delayed-release capsules should be taken before eating. Lansoprazole delayed-release capsule products SHOULD NOT BE CRUSHED OR CHEWED. In the clinical trials, antacids were used concomitantly with lansoprazole delayed-release capsules.
2.1 Recommended Dose
Indication Recommended Dose Frequency
*
†
Duodenal Ulcers
Short-Term Treatment 15 mg Once daily for 4 weeks
Maintenance of Healed 15 mg Once daily
H. pylori Eradication to Reduce the Risk of Duodenal Ulcer Recurrence*
Triple Therapy:
Lansoprazole delayed-release capsules 30 mg Twice daily (q12h) for 10 or 14 days
Amoxicillin 1 gram Twice daily (q12h) for 10 or 14 days
Clarithromycin 500 mg Twice daily (q12h) for 10 or 14 days
Dual Therapy:
Lansoprazole delayed-release capsules 30 mg Three times daily (q8h) for 14 days
Amoxicillin 1 gram Three times daily (q8h) for 14 days
Benign Gastric Ulcer
Short-Term Treatment 30 mg Once daily for up to 8 weeks
NSAID-associated Gastric Ulcer
Healing 30 mg Once daily for 8 weeks†*
Risk Reduction 15 mg Once daily for up to 12 weeks†
Gastroesophageal Reflux Disease (GERD)
Short-Term Treatment of Symptomatic GERD 15 mg Once daily for up to 8 weeks
Short -Term Treatment of Erosive Esophagitis 30 mg Once daily for up to 8 weeks‡
Pediatric
(1 to 11 years of age)
Short-Term Treatment of Symptomatic GERD and Short-Term Treatment of Erosive Esophagitis
≤ 30 kg 15 mg Once daily for up to 12 weeks†§
> 30 kg 30 mg Once daily for up to 12 weeks§
(12 to 17 years of age)
Short-Term Treatment of Symptomatic GERD
Nonerosive GERD 15 mg Once daily for up to 8 weeks
Erosive Esophagitis 30 mg Once daily for up to 8 weeks
Maintenance of Healing of Erosive Esophagitis 15 mg Once daily#
Pathological Hypersecretory Conditions Including Zollinger-Ellison Syndrome 60 mg Once daily¶
* Please refer to amoxicillin and clarithromycin full prescribing information for CONTRAINDICATIONS and WARNINGS, and for information regarding dosing in elderly and renally-impaired patients.
† Controlled studies did not extend beyond indicated duration.
‡ For patients who do not heal with lansoprazole delayed-release capsules for 8 weeks (5 to 10%), it may be helpful to give an additional 8 weeks of treatment. If there is a recurrence of erosive esophagitis, an additional 8 week course of lansoprazole delayed-release capsules may be considered.
§The lansoprazole delayed-release capsules dose was increased (up to 30 mg twice daily) in some pediatric patients after 2 or more weeks of treatment if they remained symptomatic. For pediatric patients unable to swallow an intact capsule please see Administration Options.
¶ Varies with individual patient. Recommended adult starting dose is 60 mg once daily. Doses should be adjusted to individual patient needs and should continue for as long as clinically indicated. Dosages up to 90 mg twice daily have been administered. Daily dose of greater than 120 mg should be administered in divided doses. Some patients with Zollinger-Ellison Syndrome have been treated continuously with lansoprazole delayed-release capsules for more than 4 years.
# Controlled studies did not extend beyond 12 months
Patients should be instructed that if a dose is missed, it should be taken as soon as possible. However, if the next scheduled dose is due, the patient should not take the missed dose, and should be instructed to take the next dose on time. Patients should be instructed not to take 2 doses at one time to make up for a missed dose.
2.2 Special Populations
Renal impairment patients and geriatric patients do not require dosage adjustment. However, consider dose adjustment in patients with severe liver impairment. [See Use in Specific Populations (8.5, 8.6 and 8.7]
2.3 Important Administration Information
Administration Options
Lansoprazole Delayed-Release Capsules - Oral Administration
• Lansoprazole delayed-release capsules should be swallowed whole.
• Alternatively, for patients who have difficulty swallowing capsules, lansoprazole delayed-release capsules can be opened and administered as follows:
o Open capsule.
o Sprinkle intact granules on one tablespoon of either applesauce, ENSURE pudding, cottage cheese, yogurt or strained pears.
o Swallow immediately.
• Lansoprazole Delayed-Release Capsules may also be emptied into a small volume of either apple juice, orange juice or tomato juice and administered as follows:
o Open capsule.
o Sprinkle intact granules into a small volume of either apple juice, orange juice or tomato juice (60 mL – approximately 2 ounces).
o Mix briefly.
o Swallow immediately.
o To ensure complete delivery of the dose, the glass should be rinsed with two or more volumes of juice and the contents swallowed immediately.
Lansoprazole Delayed-Release Capsules - Nasogastric Tube (≥ 16 French) Administration
• For patients who have a nasogastric tube in place, lansoprazole delayed-release capsules can be administered as follows:
o Open capsule.
o Mix intact granules into 40 mL of apple juice. DO NOT USE OTHER LIQUIDS.
o Inject through the nasogastric tube into the stomach.
o Flush with additional apple juice to clear the tube.
USE IN OTHER FOODS AND LIQUIDS HAS NOT BEEN STUDIED CLINICALLY AND IS THEREFORE NOT RECOMMENDED.